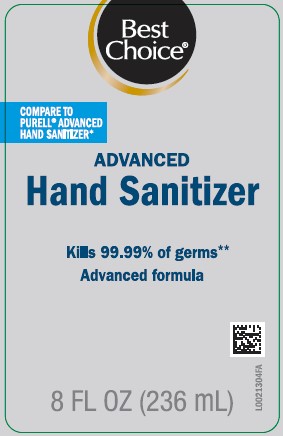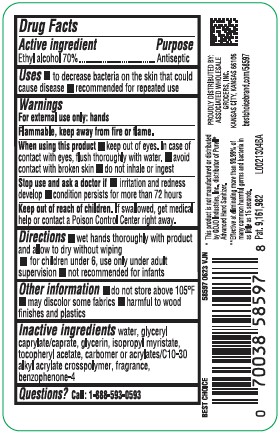 DRUG LABEL: Hand Sanitizer
NDC: 63941-008 | Form: GEL
Manufacturer: Valu Merchandisers Company
Category: otc | Type: HUMAN OTC DRUG LABEL
Date: 20260216

ACTIVE INGREDIENTS: ALCOHOL 70 mL/100 mL
INACTIVE INGREDIENTS: WATER; GLYCERYL CAPRYLATE/CAPRATE; GLYCERIN; ISOPROPYL MYRISTATE; .ALPHA.-TOCOPHEROL ACETATE; CARBOMER HOMOPOLYMER, UNSPECIFIED TYPE; CARBOMER COPOLYMER TYPE B (ALLYL PENTAERYTHRITOL CROSSLINKED); SULISOBENZONE

Best Choice 370.001/370AE
Advanced Hand Sanitizer

Active ingredient

Ethyl alcohol 70%

Purpose

Antiseptic

Uses

- to decrease bacteria on the skin that could cause disease
- recommended for repeated use

Warnings

For external use only: hands

Flammable. Keep away from fire or flame.

When using this product

- keep out of eyes. In case of contact with eyes, flush thoroughly with water.
- avoid contact with broken skin
- do not inhale or ingest

Stop use and ask a doctor if

- irritation and redness develop
- condition persists for more than 72 hours

Keep out of reach of children.

If swallowed, get medical help or contact a Poison Control Center right away.

Directions

- wet hands thoroughly with product and allow to dry without wiping
- for children under 6, use only under adult supervision
- not recommended for infants

Other information

- do not store above 105⁰ F
- may discolor some fabrics
- harmful to wood finishes and plastics

Inactive ingredients

water, glyceryl caprylate/caprate, glycerin, isopropyl myristate, tocopheryl acetate, carbomer or acrylates/C10-30 alkyl acrylate crosspolymer, fragrance, benzophenone-4

Questions?

Call 1-888-593-0593

Disclaimer

*This product is not manufactured or distributed by GOJO Industries, Inc. distributor of Purell®Advanced Hand Sanitizer.

Claim

**Effective at eliminating more than 99.99% of many common harmful germs and bacteria in as little as 15 seconds.

Adverse Reaction

PROUDLY DISTRIBUTED BY:

ASSOCIATED WHOLESALE GROCERS, INC

KANSAS CITY, KS 66106

bestchoicebrand.com/58597

Pat. 9,191,982

Principal display panel

Best Choice®

COMPARE TO PURELL®ADVANCED HAND SANITIZER*

ADVANCED

Hand Sanitizer

Kills 99.99% of germs**

Advanced formula

8 FL OZ (236 mL)